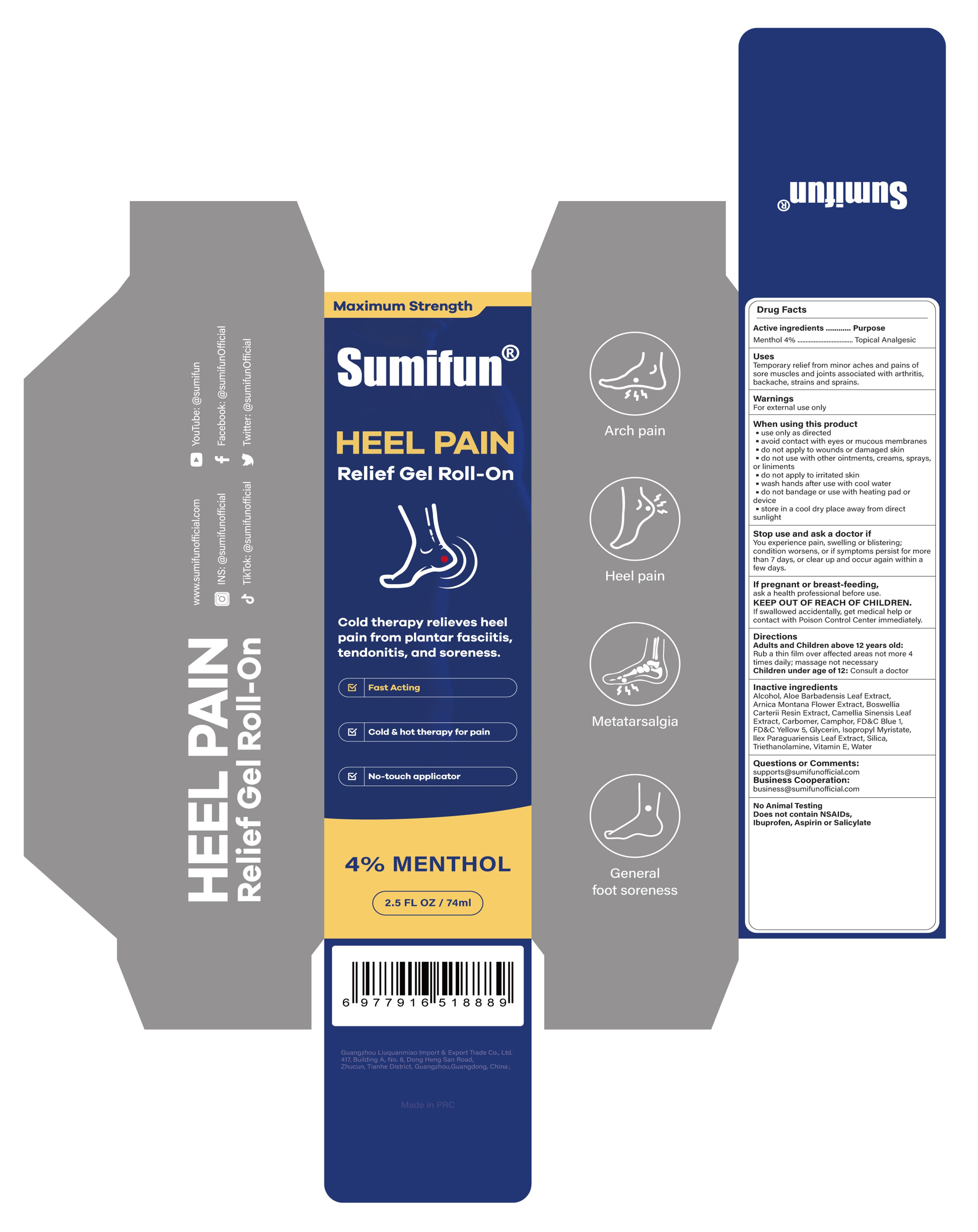 DRUG LABEL: HEEL PAIN  Relief Gel Roll-On
NDC: 84165-011 | Form: GEL
Manufacturer: Guangzhou Zhupuyou E-commerce Co., Ltd
Category: otc | Type: HUMAN OTC DRUG LABEL
Date: 20250604

ACTIVE INGREDIENTS: MENTHOL 0.04 g/1 mL
INACTIVE INGREDIENTS: ALCOHOL 95%; WATER; .ALPHA.-TOCOPHEROL, D-; TRIETHANOLAMINE; ARNICA MONTANA FLOWER; CAMELLIA SINENSIS LEAF; CAMPHOR (SYNTHETIC); ISOPROPYL MYRISTATE; OLIBANUM; GLYCERIN; ALOE BARBADENSIS LEAF; FD&C BLUE NO. 1; ILEX PARAGUARIENSIS LEAF; SILICA; FD&C YELLOW NO. 5; CARBOMER

84165-011 HEEL PAIN Relief Gel Roll-On

ACTIVE INGREDIENT

Menthol 4%

PURPOSE

Topical Analgesic

INDICATIONS AND USAGE

Temporary relief from minor aches and pains ofsore muscles and joints associated with arthritis,backache, strains and sprains.

WARNINGS

For external use only

do not apply to wounds or damaged skin
do not use with other ointments, creams, sprays
or liniments
do not apply to irritated skinwash hands after use with cool water
do not bandage or use with heating pad ordevice

WHEN USING

use only as directed
avoid contact with eyes or mucous membranes
store in a cool dry place away from directsunlight

STOP USE

You experience pain, swelling or blistering;condition worsens, or if symptoms persist for morethan 7 days, or clear up and occur again within afew days.

KEEP OUT OF REACH OF CHILDREN

If swallowed accidentally, get medical help orcontact with Poison Control Center immediately.

DOSAGE AND ADMINISTRATION

Adults and Children above 12 years old:
Rub a thin film over affected areas not more 4 times daily; massage not necessary
Children under age of 12: Consult a doctor

INACTIVE INGREDIENT

Alcohol
Aloe barbadensis leaf extract
Arnica montana flower extract
Boswellia carterii resin extract
Camellia sinensis leaf extract
Carbomer
Camphor
FD&C Blue 1
FD&C Yellow 5
Glycerin
Ilex Paraguariensis Leaf Extract
Isopropyl Myristate
Silica
Triethanolamine
Vitamin E
Water